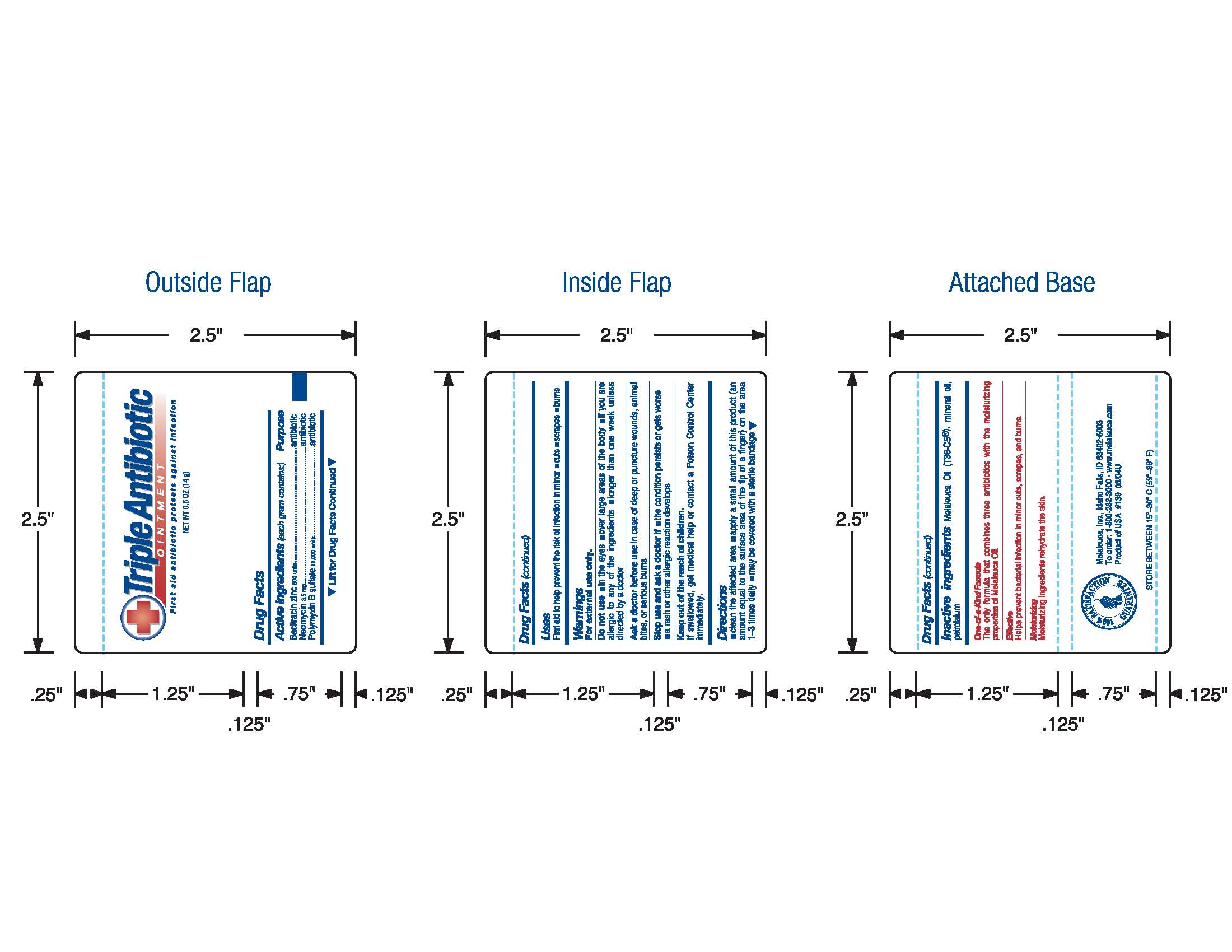 DRUG LABEL: Triple Antibiotic
NDC: 54473-578 | Form: OINTMENT
Manufacturer: Melaleuca, Inc.
Category: otc | Type: HUMAN OTC DRUG LABEL
Date: 20101231

ACTIVE INGREDIENTS: BACITRACIN ZINC 500 [iU]/1 g; NEOMYCIN 3.5 mg/1 g; POLYMYXIN B SULFATE 10000 [iU]/1 g
INACTIVE INGREDIENTS: Tea Tree Oil; MINERAL OIL; Petrolatum

Triple Antibiotic Ointment Label

Active Ingredients (each gram contains:)
Bacitracin zinc 500 units
Neomycin 3.5 mg
Polymyxin B sulfate 10,000 units

Purpose
antibiotic

Uses
First aid to help prevent the risk of infection in minor

- cuts
- scrapes
- burns

Warnings
For external use only.

Do not use

- in the eyes
- over large areas of the body
- if you are allergic to any of the ingredients
- longer than one week unless directed by a doctor

Ask a doctor
before use in case of deep or puncture wounds, animal bites, or serious burns

Stop use and ask a doctor if

- the condition persists or gets worse
- a rash or other allergic reaction develops

Keep out of reach of children.
If swallowed, get medical help or contact a Poison Control Center immediately.

Directions

- Clean the affected area
- apply a small amount of this product (an amount equal to the surface area of the tip of a finger) on the area 1-3 times daily
- may be covered with a sterile bandage

INACTIVE INGREDIENT

Inactive ingredients: Melaleuca Oil (T36-C5(R)), mineral oil, petrolatum